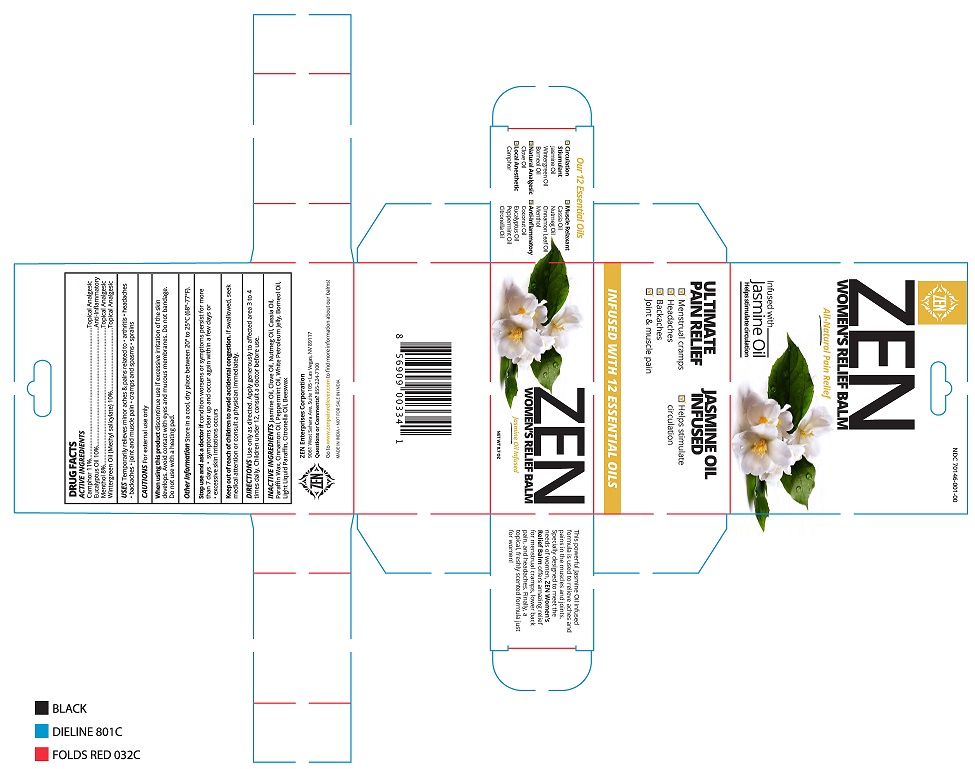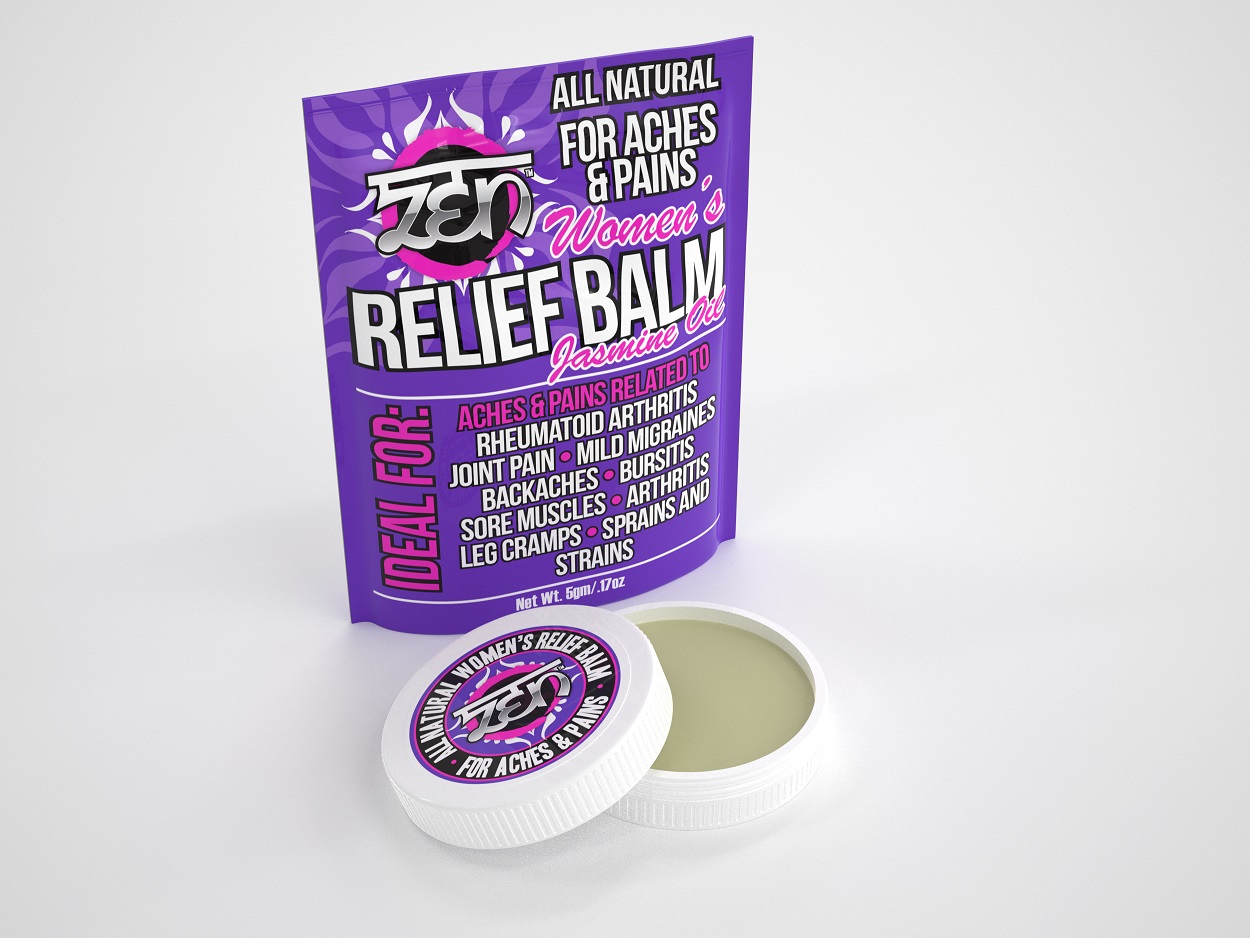 DRUG LABEL: Womens Relief Balm
NDC: 70146-001 | Form: CREAM
Manufacturer: Dr.Sankunni's Ayurvedic Research Foundation Private Limited
Category: otc | Type: HUMAN OTC DRUG LABEL
Date: 20210604

ACTIVE INGREDIENTS: CAMPHOR (NATURAL) 11 g/100 g; EUCALYPTUS OIL 10 g/100 g; MENTHOL 10 g/100 g; METHYL SALICYLATE 10 g/100 g
INACTIVE INGREDIENTS: PETROLATUM; LIGHT MINERAL OIL; YELLOW WAX; CLOVE OIL; NUTMEG OIL; CHINESE CINNAMON OIL; CINNAMON OIL; PEPPERMINT OIL; BORNEOL; CITRONELLA OIL; JASMINUM OFFICINALE FLOWER; PARAFFIN

Womens Relief Balm

Active Ingredients Purpose

Camphor 11% Topical Analgesic

Eucalyptus Oil 10% Anti-Inflammatory

Menthol 8% Topical Analgesic

Wintergreen Oil (Methyl Salicylate) 10% Topical Analgesic

PURPOSE

Uses: Temporarily relieves minor aches & pains related to

- arthritis
- backaches
- bursitis
- sore muscles
- joint pain
- leg cramps
- bruises
- sprains

Keep out of reach of children to avoid accidental ingestion.

If swallowed, get medical help or contact a poison control center immediately.

INDICATIONS AND USAGE

ZEN

for aches & pains

women's relief balm jasmine oil

ideal for:

aches & pains related to

rheumatoid arthritis

joint pain

backaches

bursitis

sore muscles

arthritis

leg cramps

sprains and strains

Directions:

- use only as directed
- apply generously to affected area 3 to 4 times daily
- children under 12, consult a doctor before use.

WARNINGS For external use only

When using this product

- discontinue use if excessive irritation of the skin develops
- avoid contact with eyes and mucus membranes
- do not bandage tightly
- do not use with heating pad

Stop use and ask a doctor if

- condition worsens or symptoms persist for more than 7 days
- symptoms clear up and occur again within a few days
- excessive skin irritation occurs

Inactive Ingredients

paraffin wax, white petroleum jelly, light liquid paraffin, beeswax, clove oil, nutmeg oil, cassia oil, cinnamon oil, peppermint oil, borneol, citronella oil, jasmine oil